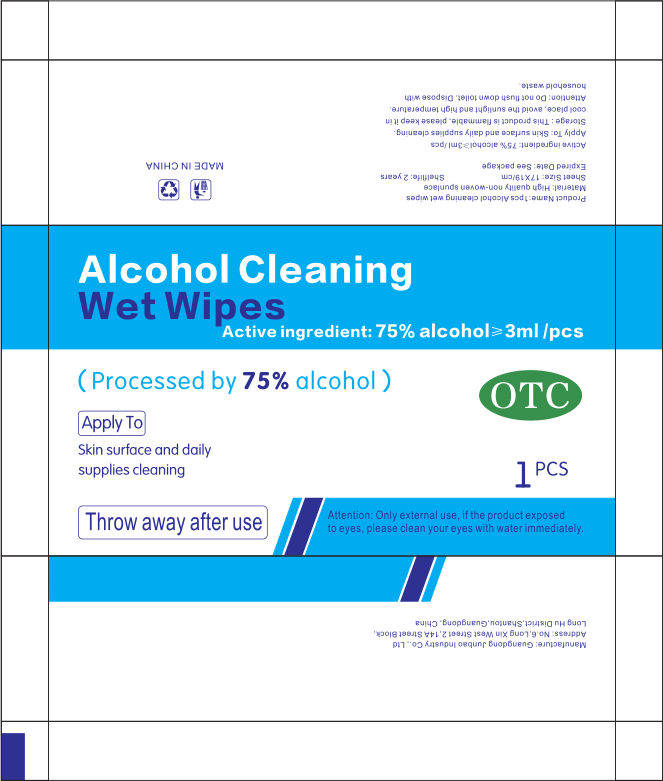 DRUG LABEL: 1pcs alcohol cleaning wet wipes
NDC: 54325-002 | Form: CLOTH
Manufacturer: Guangdong Junbao Industry Co.,Ltd
Category: otc | Type: HUMAN OTC DRUG LABEL
Date: 20200702

ACTIVE INGREDIENTS: ALCOHOL 3 mL/1 1
INACTIVE INGREDIENTS: WATER

DOSAGE AND ADMINISTRATION

please keep it in cool place

INACTIVE INGREDIENT

water

INDICATIONS AND USAGE

Draw a piece of wet paper and wipe on the surface of the skin

ACTIVE INGREDIENT

ALCOHOL

keep out of reach of children

PURPOSE

Disinfection
Sterilization
No Rinseing

WARNINGS

This product is flammable, please keep it in cool place, avoid the sunlight and high temperature.Attention: Do not flush down toilet. Dispose with household waste.